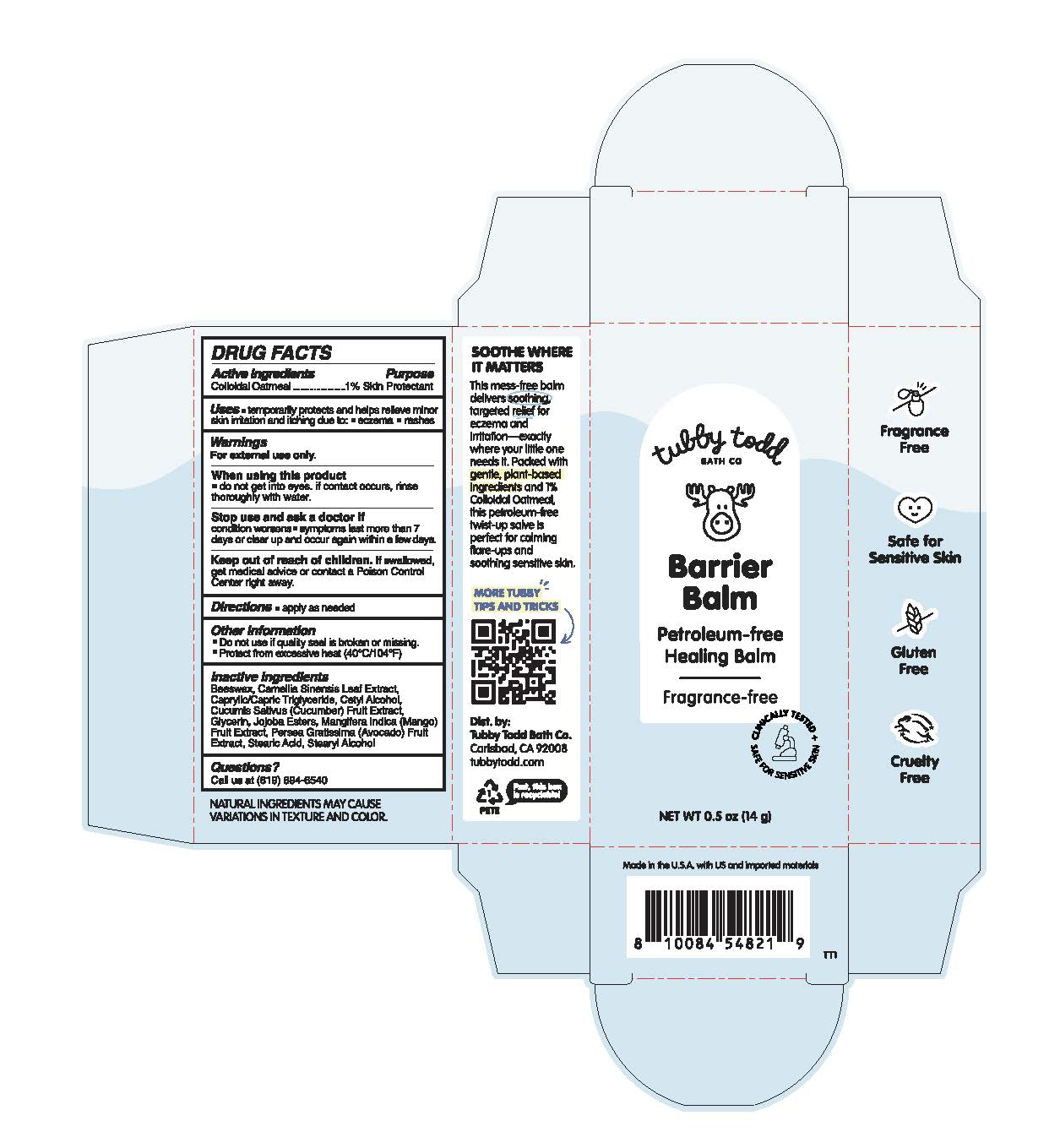 DRUG LABEL: Barrier Balm
NDC: 73088-305 | Form: SALVE
Manufacturer: Tubby Todd
Category: otc | Type: HUMAN OTC DRUG LABEL
Date: 20251107

ACTIVE INGREDIENTS: OATMEAL 1 g/100 g
INACTIVE INGREDIENTS: STEARYL ALCOHOL; BEESWAX; HYDROLYZED JOJOBA ESTERS; GLYCERIN; CAMELLIA SINENSIS LEAF; MANGIFERA INDICA (MANGO) FRUIT; CAPRYLIC/CAPRIC TRIGLYCERIDE; CETYL ALCOHOL; CUCUMIS SATIVUS (CUCUMBER) FRUIT; AVOCADO; STEARIC ACID

Barrier Balm (73088-305-01)

Drug Facts

Active ingredients

Colloidal Oatmeal 1%

Purpose

Skin protectant

Uses

• Temporarily protects and helps relieve minor skin irritation and itching due to: • eczema • rashes

Warnings

For external use only.

When using this product do not get into eyes. if contact occurs, rinse thoroughly with water.

Stop use and ask a doctor if • condition worsens • symptoms last more than 7 days or clear up and occur again in a few days.

Keep out of reach of children. If swallowed, get medical advice or contact a Poison Control Center right away.

Directions

Apply as needed

Other information

Do not use if quality seal is broken or missing. Protect from excessive heat (40°C/104°F)

Inactive ingredients

Beeswax, Camellia Sinensis Leaf Extract, Caprylic/Capric Triglyceride, Cetyl Alcohol, Cucumis Sativus (Cucumber), Fruit Extract, Glycerin, Jojoba Esters, Mangifera Indica (Mango) Fruit Extract, Persea Gratissima (Avocado) Fruit Extract, Stearic Acid, Stearyl Alcohol

Questions?

Call us at (619) 894-6540